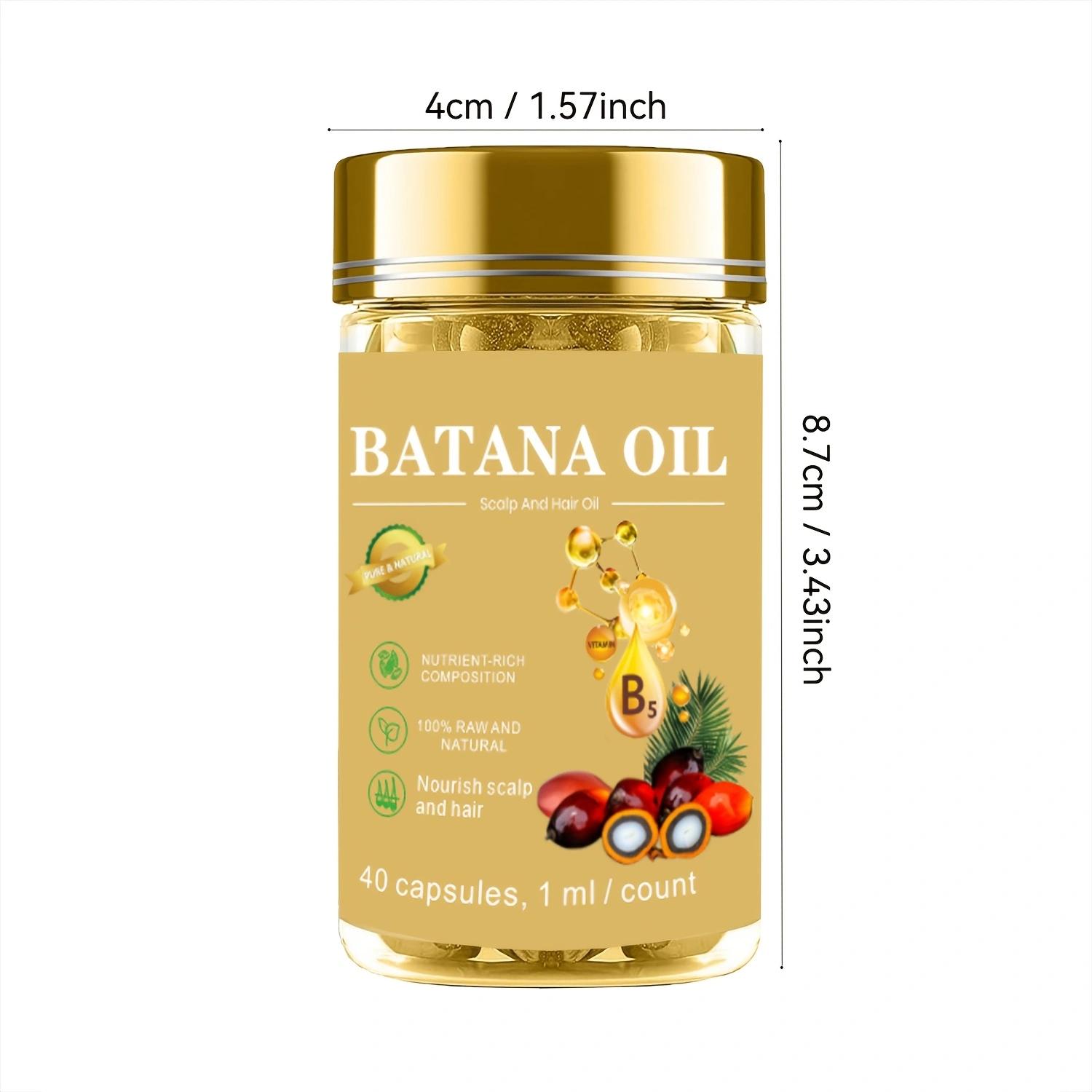 DRUG LABEL: SYBatanaOilCapsules
NDC: 84778-038 | Form: LIQUID
Manufacturer: Guangzhou Yixin Cross-border E-commerce Co., Ltd.
Category: otc | Type: HUMAN OTC DRUG LABEL
Date: 20241125

ACTIVE INGREDIENTS: ELAEIS OLEIFERA KERNEL OIL 40 g/40 mL
INACTIVE INGREDIENTS: WATER

COMPONENTS

Elaeis Oleifera Kernel Oil 40ML

PURPOSE

Effectively repairs dry, brittle and damaged hair

INDICATIONS AND USAGE

Squeeze batana oil from the capsule and apply directly to your hair or scalp, massaging it in gently to help repair damaged hair.

WARNINGS

For external use only.

If sensitive irritation occurs, please stop using and store in a cool and dry place.

DOSAGE AND ADMINISTRATION

For external use only

DO NOT USE

If you are allergic to any of the ingredients in the capsule, please avoid using this product. Common allergic reactions include rash, itching, redness, swelling, and difficulty breathing

WHEN USING

Squeeze the batana oil from the capsule and apply it directly to the hair or scalp. Massage gently and let it absorb to help repair damaged hair. For dry, rough skin, apply the oil to the skin, especially dry areas such as elbows and knees, to moisturize and repair.

Do not use on open wounds or allergic skin.

KEEP OUT OF REACH OF CHILDREN

If sxralowed, get medical help or contact a Poison Conirol Cenler ngiht away.

INACTIVE INGREDIENT

water